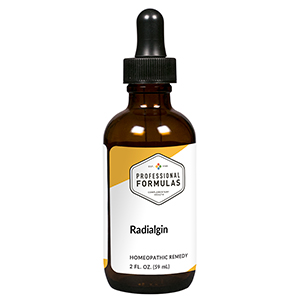 DRUG LABEL: Radialgin
NDC: 63083-6002 | Form: LIQUID
Manufacturer: Professional Complementary Health Formulas
Category: homeopathic | Type: HUMAN OTC DRUG LABEL
Date: 20190815

ACTIVE INGREDIENTS: LEMON JUICE 2 [hp_X]/59 mL; FAGOPYRUM ESCULENTUM WHOLE 2 [hp_X]/59 mL; FUCUS VESICULOSUS 2 [hp_X]/59 mL; SODIUM CATION 2 [hp_X]/59 mL; HYDRANGEA ARBORESCENS ROOT 4 [hp_X]/59 mL; CALCIUM FLUORIDE 12 [hp_X]/59 mL; SODIUM CHLORIDE 12 [hp_X]/59 mL; PHOSPHORUS 12 [hp_X]/59 mL; STRONTIUM CATION 30 [hp_X]/59 mL; URANYL NITRATE HEXAHYDRATE 30 [hp_X]/59 mL; LACTOSE, X-RAY EXPOSED (1000 RAD) 30 [hp_X]/59 mL
INACTIVE INGREDIENTS: ALCOHOL; WATER

X2

ACTIVE INGREDIENTS

Citrus limonum 2X
Fagopyrum esculentum 2X
Fucus vesiculosus 2X
Sodium alginate 2X
Hydrangea arborescens 4X
Calcarea fluorica 12X
Natrum muriaticum 12X
Phosphorus 12X
Strontium nitricum 30X, 60X
Uranium nitricum 30X, 60X
and all the following imponderables at 30X, 60X:
Cell phone
Color TV
Flat screen TV
Microwave
Wifi
X-Ray

QUESTIONS

Professional Formulas

PO Box 2034 Lake Oswego, OR 97035

INDICATIONS

For the temporary relief of itchy skin or minor rash, occasional headache, fatigue or weakness, confusion, muscle aches or pains, or sleep disturbance due to sensitivity to or exposure to microwaves, television, or other household radiation.*

PURPOSE

*Claims based on traditional homeopathic practice, not accepted medical evidence. Not FDA evaluated.

WARNINGS

Consult a doctor if condition worsens or symptoms persist. Keep out of the reach of children. In case of overdose, get medical help or contact a poison control center right away. If pregnant or breastfeeding, ask a healthcare professional before use.

Keep out of the reach of children.

PREGNANCY OR BREAST FEEDING

If pregnant or breastfeeding, ask a healthcare professional before use.

DIRECTIONS

Place drops under tongue 30 minutes before/after meals. Adults and children 12 years and over: Take 10 drops up to 3 times per day. Consult a physician for use in children under 12 years of age.

OTHER INFORMATION

Tamper resistant. If seal is broken, do not use. After opening, close container tightly and store at room temperature away from heat.

INACTIVE INGREDIENTS

20% ethanol, purified water.

LABEL

Est 1985

Professional Formulas

Complementary Health

Radialgin

Homeopathic Remedy

2 FL. OZ. (59 mL)